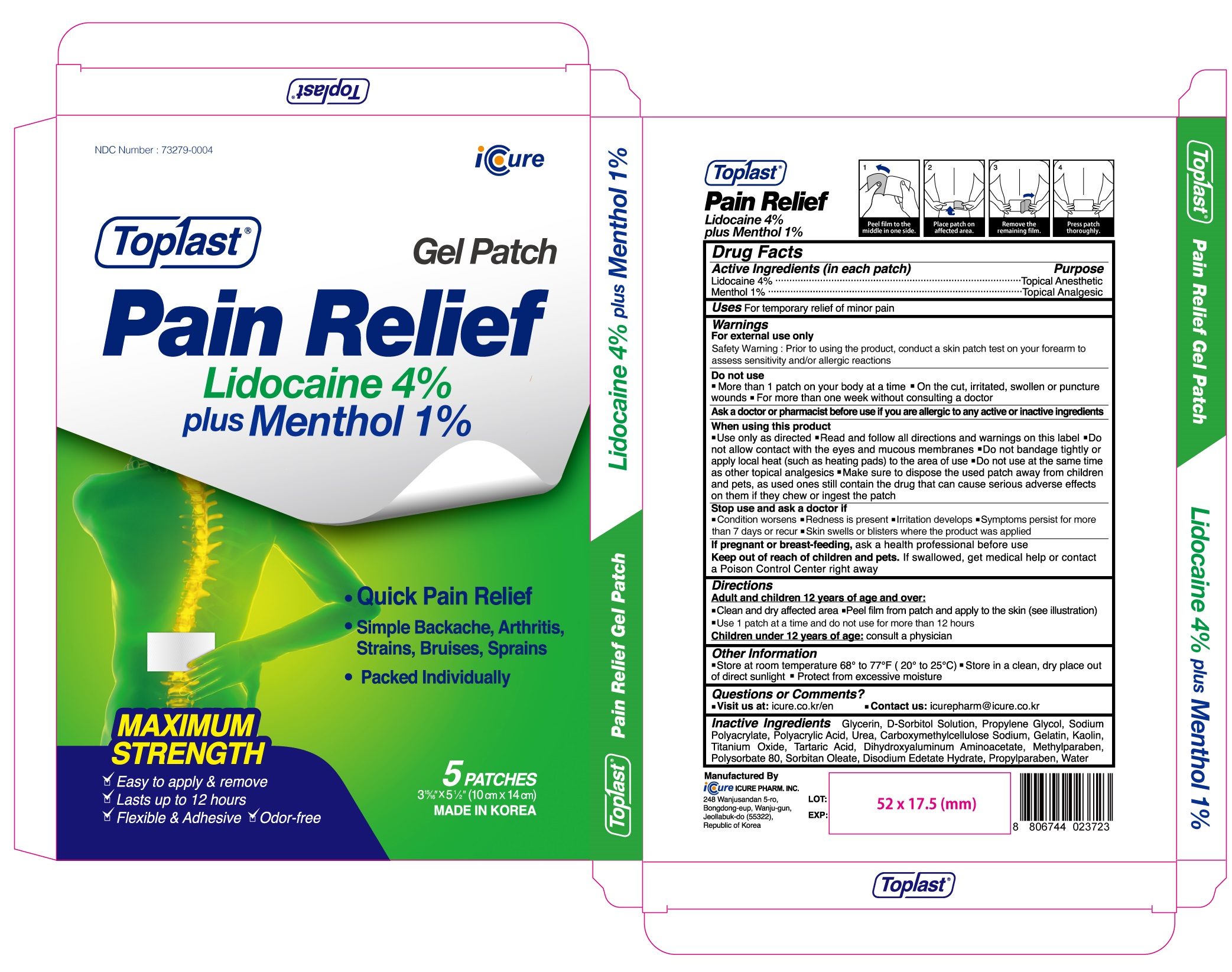 DRUG LABEL: Toplast Pain Relief Lidocaine 4percent plus Menthol 1percent
NDC: 73279-0004 | Form: PATCH
Manufacturer: Icure Pharmaceutical Inc, Wanju Factory
Category: otc | Type: HUMAN OTC DRUG LABEL
Date: 20210423

ACTIVE INGREDIENTS: Lidocaine 240 mg/1 1; Menthol 60 mg/1 1
INACTIVE INGREDIENTS: Glycerin; SORBITOL; Propylene Glycol; Urea; CARBOXYMETHYLCELLULOSE SODIUM, UNSPECIFIED; Gelatin; Kaolin; TITANIUM DIOXIDE; Tartaric Acid; Dihydroxyaluminum Aminoacetate; Methylparaben; Polysorbate 80; SORBITAN MONOOLEATE; EDETATE DISODIUM; Propylparaben; Water

Drug Facts

ACTIVE INGREDIENTS (in each patch)

Lidocaine 4%
Menthol 1%

INACTIVE INGREDIENTS

Glycerin, D-Sorbitol Solution, Propylene Glycol, Sodium Polyacrylate, Polyacrylic Acid, Urea, Carboxymethylcellulose Sodium, Gelatin, Kaolin, Titanium Oxide, Tartaric Acid, Dihydroxyaluminum Aminoacetate, Methylparaben, Polysorbate 80, Sorbitan Oleate, Disodium Edetate Hydrate, Propylparaben, Water

PURPOSE

Topical Anesthetic
Topical Analgesic

WARNINGS

For external use only
Safety Warning : Prior to using the product, conduct a skin patch test on your forearm to assess sensitivity and/or allergic reactions
--------------------------------------------------------------------------------------------------------
Do not use
■ More than 1 patch on your body at a time ■ On the cut, irritated, swollen or puncture wounds ■ For more than one week without consulting a doctor
--------------------------------------------------------------------------------------------------------
Ask a doctor or pharmacist before use if you are allergic to any active or inactive ingredients
--------------------------------------------------------------------------------------------------------
When using this product
■ Use only as directed ■ Read and follow all directions and warnings on this label ■ Do not allow contact with the eyes and mucous membranes ■ Do not bandage tightly or apply local heat (such as heating pads) to the area of use ■ Do not use at the same time as other topical analgesics ■ Make sure to dispose the used patch away from children and pets, as used ones still contain the drug that can cause serious adverse effects on them if they chew or ingest the patch
--------------------------------------------------------------------------------------------------------
Stop use and ask a doctor if
■ Condition worsens ■ Redness is present ■ Irritation develops ■ Symptoms persist for more than 7 days or recur ■ Skin swells or blisters where the product was applied
--------------------------------------------------------------------------------------------------------
If pregnant or breast-feeding, ask a health professional before use
Keep out of reach of children and pets. If swallowed, get medical help or contact a Poison Control Center right away

Keep out of reach of children and pets

If swallowed, get medical help or contact a Poison Control Center right away

Uses

For temporary relief of minor pain

Directions

Adult and children 12 years of age and over :
■ Clean and dry affected area ■ Peel film from patch and apply to the skin (see illustration) ■ Use 1 patch at a time and do not use for more than 12 hours
Children under 12 years of age : consult a physician

Other Information

■ Store at room temperature 68° to 77°F (20° to 25°C) ■ Store in a clean, dry place out of direct sunlight ■ Protect from excessive moisture

Questions or Comments

■ Visit us at : icure.co.kr/en ■ Contact us : icurepharm@icure.co.kr